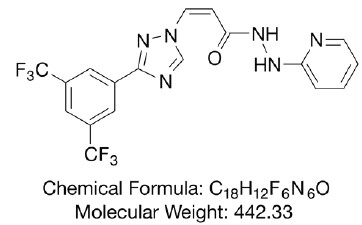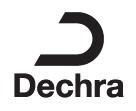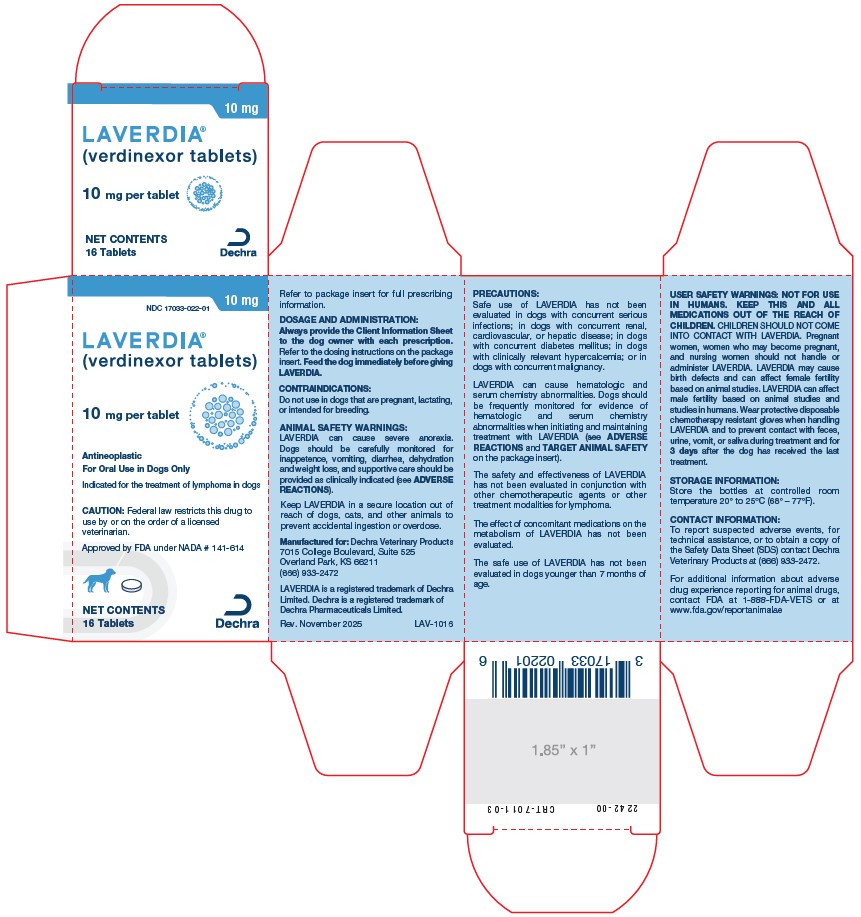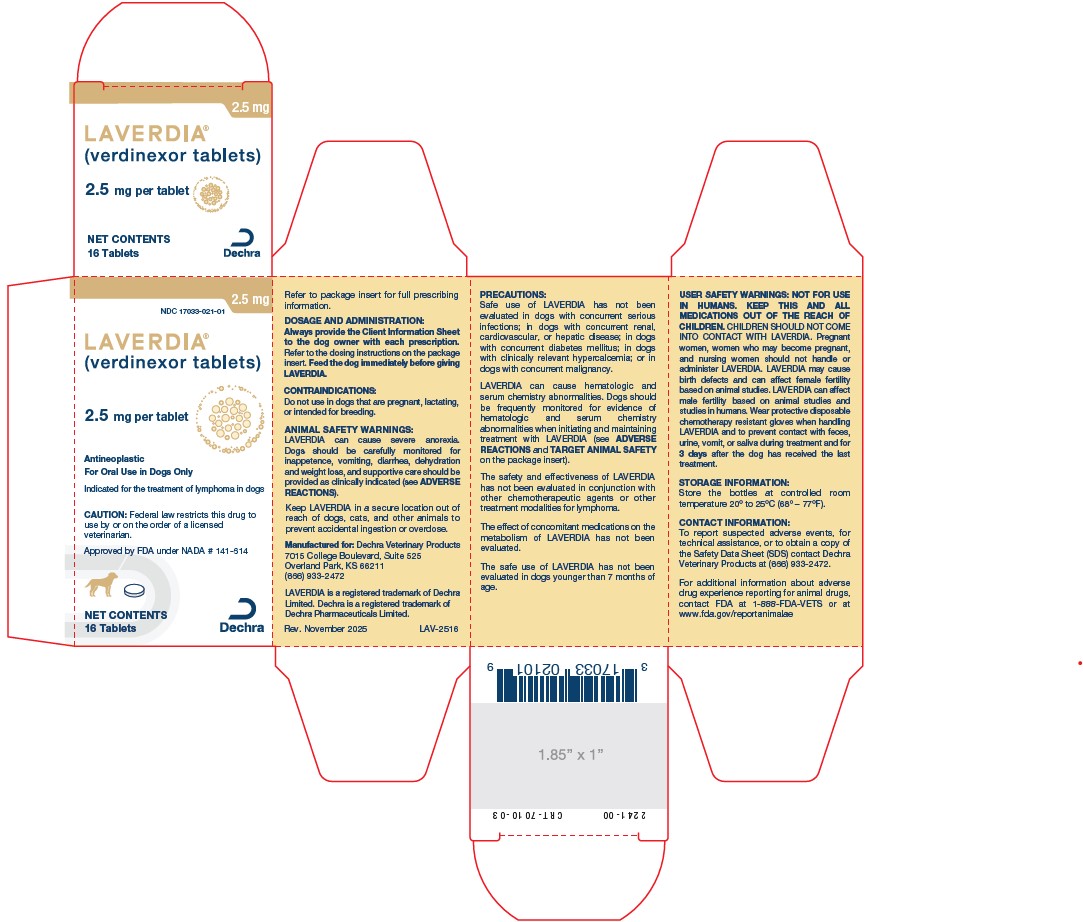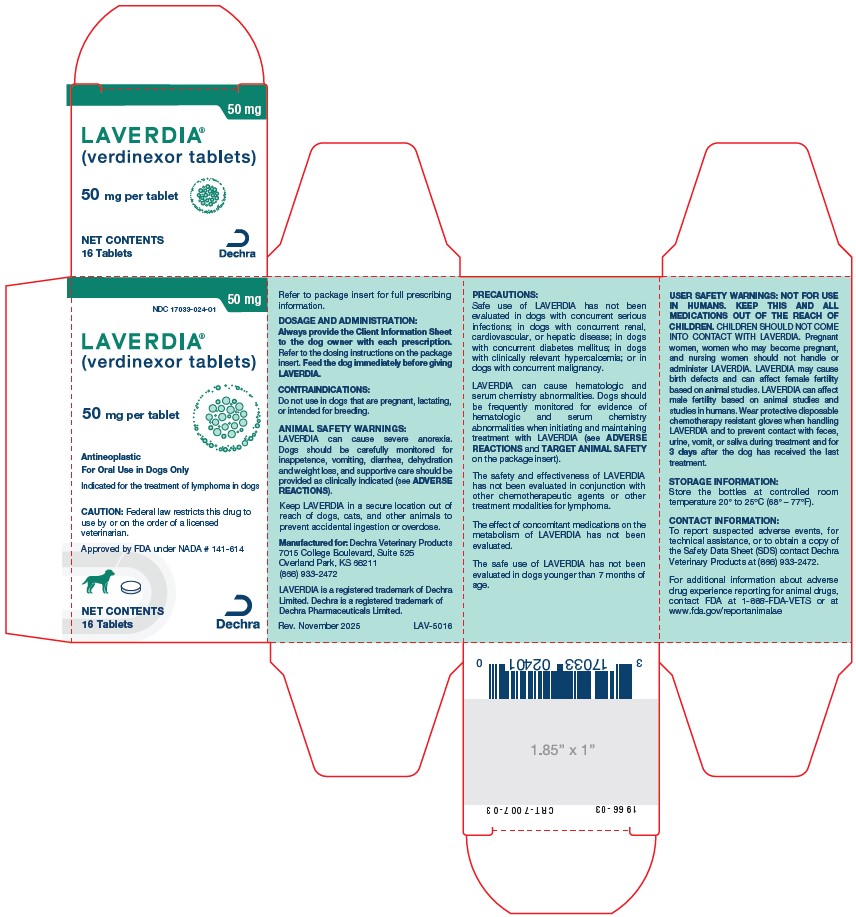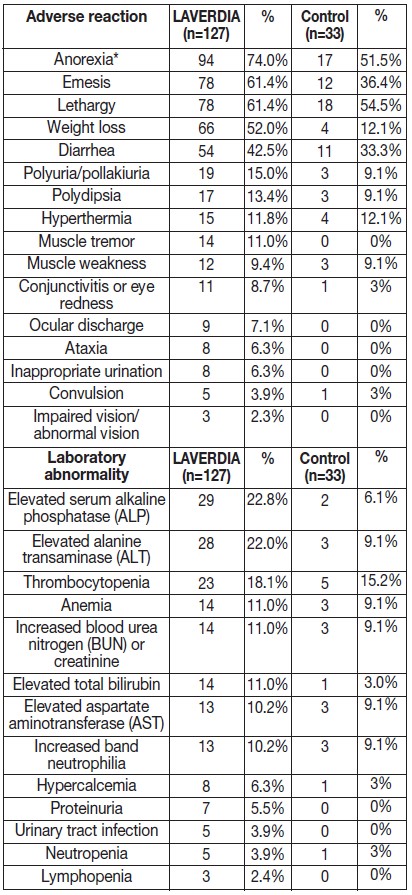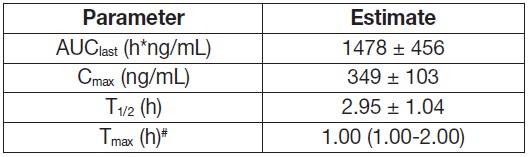 DRUG LABEL: Laverdia
NDC: 17033-021 | Form: TABLET, COATED
Manufacturer: Dechra Veterinary Products, LLC
Category: animal | Type: PRESCRIPTION ANIMAL DRUG LABEL
Date: 20260209

ACTIVE INGREDIENTS: VERDINEXOR 2.5 mg/1 1

LAVERDIA®
(verdinexor tablets)

2.5 mg · 10 mg · 22.5 mg · 50 mg

Coated Tablets

Antineoplastic

For oral use in dogs only

CAUTION: Federal law restricts this drug to use by or on the order of a licensed veterinarian.

DESCRIPTION

DESCRIPTION: LAVERDIA (verdinexor tablets) is a selective inhibitor of nuclear export (SINE) that blocks chromosome region maintenance 1 (CRM1).

LAVERDIA has the following structural formula:

INDICATION:

LAVERDIA is indicated for the treatment of lymphoma in dogs.

DOSAGE AND ADMINISTRATION:

Always provide the Client Information Sheet to the dog owner with each prescription.

Dosing Instructions:

1. Feed the dog immediately before giving LAVERDIA.

2. Wear protective disposable chemotherapy resistant gloves when handling LAVERDIA (see USER SAFETY WARNINGS).

3. Use an appropriate combination of tablets to administer the dose:

a) Administer LAVERDIA at an initial dose of 1.25 mg/kg administered orally twice per week (e.g., Monday and Thursday or Tuesday and Friday) with at least 72 hours between doses.

b) If tolerated after 2 weeks, increase the dose of LAVERDIA to 1.5 mg/kg twice per week with at least 72 hours between doses.

c) Dose reductions of 0.25 mg/kg to a minimum dose of 1 mg/kg twice per week with at least 72 hours between doses or dose interruptions may be considered if the dog has adverse reactions (see ANIMAL SAFETY WARNINGS, PRECAUTIONS, and ADVERSE REACTIONS).

4. Do not split or crush tablets.

CONTRAINDICATIONS:

Do not use in dogs that are pregnant, lactating or intended for breeding. LAVERDIA is a possible teratogen and can affect female and male fertility. Laboratory studies in the rat have shown reduced fertility, embryotoxicity, teratogenicity and maternal toxicity. Administration of LAVERDIA caused degeneration/atrophy and vacuolation in the seminiferous tubules and oligospermia in the epididymides in male dogs in the margin of safety study (see TARGET ANIMAL SAFETY).

WARNINGS:

USER SAFETY WARNINGS:

NOT FOR USE IN HUMANS. KEEP THIS AND ALL MEDICATIONS OUT OF THE REACH OF CHILDREN. CHILDREN SHOULD NOT COME INTO CONTACT WITH LAVERDIA. Children should not come in contact with the feces, urine, vomit, or saliva of treated dogs.

Pregnant women, women who may become pregnant, and nursing women should not handle or administer LAVERDIA or come in contact with the feces, urine, vomit, or saliva from LAVERDIA-treated dogs. Based on animal studies, LAVERDIA can cause birth defects and affect female fertility.

LAVERDIA can affect male fertility based on animal studies and studies in humans.

Wear protective disposable chemotherapy resistant gloves when handling LAVERDIA to avoid exposure to drug.

Wear protective disposable chemotherapy resistant gloves to prevent direct contact with moistened, broken, or crushed LAVERDIA tablets.

Wear protective disposable chemotherapy resistant gloves to prevent contact with feces, urine, vomit, and saliva during treatment and for 3 days after the dog has received the last treatment. Place all waste material in a plastic bag and seal before general disposal. Wash hands immediately and thoroughly with soap and water if contact with the feces, urine, vomit, or saliva from LAVERDIA-treated dogs occurs.

Any items that come in contact with feces, urine, vomit, or saliva should not be washed with other laundry during treatment and for 3 days after the last treatment with LAVERDIA.

Wear protective disposable chemotherapy resistant gloves when handling the dog’s toys, food bowl, and water bowl. Wash food and water bowls separately from other items during treatment and for 3 days after the dog has received the last treatment.

If LAVERDIA is accidentally ingested, or if there is significant contact with feces, urine, vomit, or saliva of dogs during treatment or within 3 days after the last treatment without proper precautions, seek medical advice immediately.

It is important to show the treating physician a copy of the package insert, label, or client information sheet.

Special instructions for handling and administering the product

• It is recommended that LAVERDIA be administered under the supervision of, or in consultation with, a veterinarian experienced in the use of cancer therapeutic agents.

• Use standard measures for the safe handling of all chemotherapeutic drugs. Refer to Occupational Safety and Health Administration (OSHA) for appropriate guidelines, recommendations, and regulations for handling antineoplastic agents.

• Do not eat, drink or smoke while handling the product.

• Do not store near food, in or near a food preparation area, or with medications intended for use in humans.

Skin contact

• In case of contact with skin, wash the affected area immediately and thoroughly with soap and water.

Accidental eye exposure

• Rinse eyes with large amounts of tap water (use eyewash station if present) for 10 minutes while holding back the eyelid.

• Remove contact lenses.

• Seek medical advice immediately and show the package insert or label to the physician.

Accidental oral exposure or ingestion

• Seek medical advice immediately and show the package insert or label to the physician.

ANIMAL SAFETY WARNINGS:

LAVERDIA can cause severe anorexia. Dogs should be carefully monitored for inappetence, vomiting, diarrhea, dehydration and weight loss, and supportive care should be provided as clinically indicated (see ADVERSE REACTIONS).

In the studies used to support approval, appetite stimulants, anti-nausea medication, and corticosteroids (prednisone) were found to reduce the incidence of anorexia and gastrointestinal adverse reactions associated with LAVERDIA.

Keep LAVERDIA in a secure location out of reach of dogs, cats, and other animals to prevent accidental ingestion or overdose.

PRECAUTIONS:

Safe use of LAVERDIA has not been evaluated in dogs with concurrent serious infections; in dogs with concurrent renal, cardiovascular, or hepatic disease; in dogs with concurrent diabetes mellitus; in dogs with clinically relevant hypercalcemia; or in dogs with concurrent malignancy.

LAVERDIA can cause hematologic and serum chemistry abnormalities. Dogs should be frequently monitored for evidence of hematologic and serum chemistry abnormalities when initiating and maintaining treatment with LAVERDIA (see ADVERSE REACTIONS and TARGET ANIMAL SAFETY).

The safety and effectiveness of LAVERDIA has not been evaluated in conjunction with other chemotherapeutic agents or other treatment modalities for lymphoma.

The effect of concomitant medications on the metabolism of LAVERDIA has not been evaluated.

The safe use of LAVERDIA has not been evaluated in dogs younger than 7 months of age.

The primary metabolism of LAVERDIA in vitro and in vivo is thought to be inactivation by glutathione (GSH) conjugation. Therefore, administration of LAVERDIA with drugs which undergo substantial GSH conjugation (e.g., acetaminophen) should be minimized.

ADVERSE REACTIONS:

A randomized, masked, controlled, multicenter clinical field study evaluated the effectiveness and safety of LAVERDIA for the treatment of lymphoma. One hundred and twenty-seven dogs received at least one dose of LAVERDIA. Thirty-three dogs received control tablets.

The Veterinary Cooperative Oncology Group - common terminology criteria for adverse events (VCOG-CTCAE) definitions^1 were used to grade the adverse reactions observed:

Grade 1 (mild), Grade 2 (moderate), Grade 3 (severe), Grade 4 (life-threatening), and Grade 5 (death or euthanasia). Most adverse reactions during the study were Grade 1 or 2.

The adverse reactions observed in the study and number of dogs experiencing each adverse reaction are summarized in Table 1 below.

Table 1. Adverse Reactions Reported During the Field Study

* Of the dogs who had anorexia, 53/94 (56%) in the LAVERDIA group and 5/17 (29%) in the control group received a concomitant medication added to improve appetite.

During the study, additional reported adverse reactions for hematologic and serum chemistry abnormalities included neutrophilia, leukocytosis, leukopenia, hypokalemia, hypochloremia.

Serious Adverse Reactions:

Serious adverse events (SAEs) were reported in 22% (28 of 127) dogs in the LAVERDIA group and 15.2% (5 of the 33) dogs in the control group. Twenty-two dogs in the LAVERDIA group and 4 dogs in the control group were euthanized or died. SAEs reported in other dogs in the LAVERDIA group included thrombocytopenia (one dog), pleural effusion (two dogs), elevated total bilirubin (one dog), neutropenia (one dog), and ventricular arrythmias/swollen face/collapse (one dog). In the control group, one dog had necrosis of the skin on tail secondary to self-trauma.

Conditional Approval Experience:

LAVERDIA was conditionally approved and marketed from 2021-2025 under the proprietary name LAVERDIA-CA1. The following adverse events
were voluntarily reported for LAVERDIA-CA1 during the conditional approval: anemia, polyuria/pollakiuria, leukocytosis, neutrophilia, muscle weakness, and lymphopenia.

CONTACT INFORMATION:

To report suspected adverse events, for technical assistance, or to obtain a copy of the Safety Data Sheet (SDS) contact Dechra Veterinary Products at 1-866-933-2472.

For additional information about adverse drug experience reporting for animal drugs, contact FDA at 1-888-FDA-VETS or at www.fda.gov/reportanimalae

INFORMATION FOR DOG OWNERS:

Always provide the Client Information Sheet with each prescription and review it with the dog owner or person responsible for care of the dog. Advise dog owners about possible adverse reactions, when to contact a veterinarian, how to handle and administer the product, and how to clean up any feces, urine, vomit, or saliva from dogs treated with LAVERDIA. The Client Information Sheet also contains warnings for humans and what to do in case of accidental human exposure to LAVERDIA.

CLINICAL PHARMACOLOGY:

Mechanism of action:

Verdinexor is a reversible, selective inhibitor of nuclear export (SINE) that specifically blocks chromosome region maintenance 1 (CRM1), also known as exportin 1 (XPO1). Verdinexor inhibits the export of tumor suppressor proteins (TSP) and growth regulatory proteins (GRP) from the nucleus where they carry out their normal functions; it is selectively cytotoxic for cells with genomic damage (i.e. for tumor cells).

Pharmacokinetics:

Following oral administration of a non-final formulation of verdinexor three times per week for 13 weeks to fed healthy young adult Beagle dogs, overall mean exposure in terms of area under the plasma concentration time curve from time zero to the last quantifiable plasma concentration (AUClast) and maximum plasma concentration (Cmax) showed an increase from 1.25 mg/kg to 1.5 mg/kg; however, exposure at 1.75 mg/kg was either similar or lower than exposure for the 1.5 mg/kg dose group on both evaluation days. The increase in exposure as assessed by dose normalized AUClast and dose normalized Cmax was approximately dose proportional from 1.25 mg/kg to 1.5 mg/kg and less than dose proportional from 1.5 mg/kg to 1.75 mg/kg in males on both evaluation days. In females, the increase in AUClast and Cmax was greater than dose proportional from 1.25 mg/kg to 1.5 mg/kg and there was minimal increase in exposure from 1.5 mg/kg to 1.75 mg/kg on both evaluation days.

Inter-animal variability was relatively high across all dose groups (%CV ranging from 16% to 81% for AUClast); therefore, pharmacokinetic differences or trends should be interpreted cautiously.

Following oral administration of a non-final formulation of verdinexor to fed and fasted dogs, there was a significant food effect on the pharmacokinetics of verdinexor with a 3-fold and 5-fold increase in AUC and Cmax, respectively, when verdinexor was administered orally in the presence of food. Time to reach Cmax (Tmax) was markedly more variable (1-18 hour) when dogs were dosed under fasted conditions as compared to when verdinexor was administered under fed conditions (1.1-2.5 hour).

Table 2. Arithmetic mean (± standard deviation) of verdinexor pharmacokinetic parameters following the first administration of a non-final formulation of verdinexor (maximum proposed label dose 1.5 mg/kg body weight) in fed male and female healthy young adult Beagle Dogs

AUClast = area under the curve from the time of dosing to the last quantifiable plasma concentration
Cmax = maximum plasma concentration
T1/2 = half-life
Tmax = time to maximum plasma concentration
#Median (range)

EFFECTIVENESS:

The effectiveness and safety of LAVERDIA for the treatment of lymphoma was evaluated in a randomized, controlled, masked, multicenter clinical field study. LAVERDIA was compared to control (identical tablets without verdinexor) using time to progression (TTP) as the primary endpoint. Progression was monitored at Days 7, 14, 28, 42, and 56. Progression was defined as the time from Day 0 to progressive disease (PD) for target and non-target lesions using assessment by a modified response evaluation criteria for peripheral nodal lymphoma in dogs^2. The modification accommodated dogs that had an initial response to treatment and demonstrated clinical benefit despite lymph node (the target lesion) enlargement.

One hundred and sixty (160) dogs were enrolled and randomly assigned to treatment with either LAVERDIA (n=127) or control (n=33). LAVERDIA was administered as described in the DOSAGE AND ADMINISTRATION section with food or immediately after a meal. The population included dogs with B-cell (80.6% of dogs) or T-cell lymphoma (18.3%) that were naïve to chemotherapy (60% of dogs) or relapsed after chemotherapy (40%), aged 3 to 14 years old, weighing between 9.3 and 72.7 kg, with the most common breeds being mixed breeds, Labrador retriever, and German Shepherd. Use of concomitant appetite stimulants was allowed. If no response to appetite stimulants occurred, prednisone administered at 0.5-1 mg/kg per day was allowed.

Effectiveness was evaluated in 134 dogs (106 dogs in the LAVERDIA group and 28 in control). Including the administration of prednisone as a covariate in the statistical model, the TTP of dogs treated with LAVERDIA was statistically significantly longer (p-value = 0.011) than that of dogs treated with control. Time to progression was 37 days in the LAVERDIA group (with a 95% confidence interval of 29 to 57 days) and 23 days in the control group (with a 95% confidence interval of 14 to 30 days).

Thirty-one (29.2%) dogs in the LAVERDIA group completed the 56-day study while 2 (7.1%) dogs in the control group completed the study. The primary reason that dogs did not complete the study was due to progressive disease, adverse events, and/or death.

Concomitant medications were used primarily for gastrointestinal adverse events or sedation for diagnostics during the study. The most commonly used concomitant medications included maropitant, prednisone, capromorelin, butorphanol, metronidazole, ondansetron, gabapentin, dexmedetomidine, trazadone, atipamezole, isotonic solutions, amoxicillin and clavulanic acid, and heartworm, flea, and tick preventives.

TARGET ANIMAL SAFETY:

In a 13-week margin of safety study, 32 healthy Beagle dogs (4/sex/group), approximately 7 months old at study initiation, were administered
LAVERDIA at either 0, 1.0, 1.5, or 1.75 mg/kg of body weight 3 times a week (Monday, Wednesday, and Friday). Dogs in the control group were sham-dosed. Dogs were fed prior to dosing. All dogs survived to study termination.

Dose-dependent LAVERDIA-related clinical findings included vomiting, inappetence, decreased body condition, decreased body weight, loss of skin elasticity, lacrimation, slight depression, and slight decrease of forelimb strength.

Non-dose-dependent LAVERDIA-related findings included abnormal feces (soft, watery, or mucoid feces), excessive shedding, and sparse hair.

Dogs in the 1.0 mg/kg group and dogs in the 1.5 and 1.75 mg/kg groups had lower body weight values, starting on study days 28 and 21 respectively, that continued to the end of the study compared to control dogs.

Dose-dependent LAVERDIA-related clinical pathology findings included decreases in chloride and increases in fibrinogen. Non-dose-dependent LAVERDIA-related clinical pathology findings included decreases in lymphocytes, eosinophils, and monocytes, and increases in albumin and blood urea nitrogen.

Dose-dependent organ weight findings in the dogs administered LAVERDIA included lower testes, thymus, and thyroid/parathyroid gland weights. Dose-dependent histopathological findings in the dogs administered LAVERDIA included lesions in the testes and epididymides (moderate to marked seminiferous tubules degeneration/atrophy, minimal to moderate vacuolation, and minimal Leydig cell hypertrophy in the testes; and severe oligospermia/germ cell debris in the epididymides) and in the thymus (minimal to mild cortical lymphoid depletion).

HOW SUPPLIED:

LAVERDIA (verdinexor tablets) is presented as immediate release coated tablets in four dosage strengths, 2.5 mg, 10 mg, 22.5 mg, and 50 mg. Each tablet strength is supplied in a 16-count and 50-count HDPE bottle with a heat sealed, child-resistant cap and a desiccant included in each bottle.

DISPOSAL:

Dispose of any unused product or waste materials in accordance with proper procedures for cytotoxic drugs.

STORAGE INFORMATION:

Store the bottles at controlled room temperature 20° to 25°C (68° – 77°F).

REFERENCES:

1. Veterinary Cooperative Oncology Group- Common Terminology Criteria for Adverse Events (VCOG-CTCAE v2) following investigational therapy in dogs and cats. Vet Compar Oncol. 2021, Vol.19(2), p.311-352.

2. Response evaluation criteria for peripheral nodal lymphoma in dogs (v1.0) - a Veterinary Cooperative Oncology Group (VCOG) consensus document. Vail DM, Michels GM, Khanna C, Selting KA, London CA; Veterinary Cooperative Oncology Group. Vet Compar Oncol. 2010; 8(1), p. 28-37.

Laverdia is a registered trademark of Dechra Limited. Dechra is a registered trademark of Dechra Pharmaceuticals Limited.

Manufactured for:

Dechra Veterinary Products, LLC
7015 College Boulevard, Suite 525, Overland Park, KS 66211

Product inquiries should be directed to Dechra Veterinary Products, (866) 933-2472.

Approved by FDA under NADA # 141-614

Issued: January 2026

1 8 9 4 - 0 3 P I N - 7 0 0 1 - 0 9

Client Information Sheet

LAVERDIA®
(verdinexor tablets)

The client information sheet contains important information about LAVERDIA (verdinexor tablets). You should read this information before you start giving your dog LAVERDIA and review it each time the prescription is refilled as there may be new information. This sheet is provided only as a summary and does not take the place of instructions from your veterinarian. Talk with your veterinarian if you do not understand any of this information or if you want to know more about LAVERDIA.

What is LAVERDIA?
LAVERDIA is an FDA approved drug to treat lymphoma in dogs. The active ingredient in LAVERDIA is verdinexor, a substance that works by preventing tumor suppressing proteins from leaving the nucleus of cells, resulting in disruption of cancer cell survival and eventual cancer cell death.

What do I need to tell my veterinarian before my dog is treated with LAVERDIA?
Tell your veterinarian:
• About other medications your dog is taking, including prescription drugs, over the counter drugs, heartworm preventatives, flea and tick medications, and vitamins and supplements, including herbal supplements.
• About your dog’s previous or current medical conditions, including any infection.
• If your dog is pregnant, nursing puppies, or you intend to breed him/her.

How is my dog given LAVERDIA?
• ALWAYS WEAR GLOVES when handling LAVERDIA and its packaging. See the Handling Instructions section (on the reverse side of this sheet) to learn more about safely administering LAVERDIA to your dog.
• LAVERDIA is given by oral administration (by mouth) to dogs.
• Feed your dog a small meal immediately before giving LAVERDIA.
• LAVERDIA may be hidden inside a treat but be certain your dog swallows the entire tablet(s). It is not recommended that tablets be placed directly in a meal/food bowl as it may be difficult to determine if they have been consumed if the entire meal is not consumed by your dog.
• Follow your veterinarian’s instructions for how much and how often to give LAVERDIA. Your dog may need to take a combination of different tablet sizes to receive the correct dose of LAVERDIA. Give all tablets at the same time. Do not change this dose or regimen without consulting with your veterinarian.
• Give each dose of LAVERDIA at least 72 hours apart (for example, give on Monday and Thursday or Tuesday and Friday).
• If your dog misses a dose of LAVERDIA, do not make up the dose. Instead, simply give the dose on the next regularly scheduled day. Be sure to tell your veterinarian about any missed doses or any difficulty with giving the tablets.

How will LAVERDIA affect my dog’s cancer?
LAVERDIA is intended to treat your dog’s cancer. Frequent check-ups by your veterinarian are necessary to determine whether your dog is responding to treatment, and to decide whether your dog should continue to receive LAVERDIA.

What are some possible side effects of LAVERDIA?
LAVERDIA may cause side effects, even at the prescribed dose. Serious side effects can occur, with or without warning.

The most frequent side effects are:
• Decreased/Loss of appetite
• Vomiting
• Lethargy
• Weight Loss
• Diarrhea

There are other side effects that may occur. For more
information about side effects ask your veterinarian.

Stop LAVERDIA immediately and contact your veterinarian if you notice any of the following changes in your dog:
• Refusal to eat for more than 1 day
• Repeated vomiting or diarrhea
• Lethargy
• If your dog experiences other changes that concern you

This client information sheet gives the most important information about LAVERDIA. For more information about LAVERDIA, talk to your veterinarian.

To report a suspected adverse reaction (side effect) call Dechra Veterinary Products at 866-933-2472.

For additional information about adverse drug experience reporting for animal drugs, contact FDA at 1-888-FDA-VETS or at www.fda.gov/reportanimalae

See reverse side for HANDLING INSTRUCTIONS

HANDLING INSTRUCTIONS:

What do I need to know to handle LAVERDIA (verdinexor tablets) safely?
ALWAYS WEAR GLOVES when handling LAVERDIA and its packaging. Because LAVERDIA is an anti-cancer drug, extra care must be taken when handling the tablets, giving the drug to your dog, and cleaning up after your dog.
• LAVERDIA is not for use in humans.
• Do not eat, drink or smoke while handling the product.
• Keep LAVERDIA in a secure storage area:
o Out of the reach of children. Children should not come in contact with LAVERDIA.
o Out of reach of dogs, cats, and other animals to prevent accidental ingestion or overdose.
• Do not store near food or near a food preparation area, or with medications intended for use in humans.
• Pregnant women, women who may become pregnant, and nursing women should not handle or administer LAVERDIA or come in contact with the feces, urine, vomit, or saliva from LAVERDIA-treated dogs.
• LAVERDIA may harm an unborn baby. For pregnant and nursing women, accidental ingestion of LAVERDIA may have adverse effects on pregnancy or the nursing baby.
• LAVERDIA may affect female and male fertility.

How to minimize exposure to the active ingredient when handling LAVERDIA?
ALWAYS WEAR GLOVES when handling LAVERDIA and its packaging. The following handling procedures will help to minimize exposure to the active ingredient in LAVERDIA for you and other members of your household:
• Anyone who administers LAVERDIA to your dog should wear protective chemotherapy resistant gloves when handling LAVERDIA. Check with your veterinarian to ensure you have the appropriate gloves.
• Minimize the number of people handling LAVERDIA.
• When you or others are handling LAVERDIA tablets:
o Do not split or crush the tablets because this will disrupt the protective film coating.
o LAVERDIA tablets should be administered to your dog immediately after they are removed from the bottle.
o Protective disposable chemotherapy resistant gloves should be worn if handling broken or moistened tablets. If your dog spits out the LAVERDIA tablet, the tablet will be moistened and should be handled with protective disposable chemotherapy resistant gloves.
o If the LAVERDIA tablet is “hidden” in a treat, make sure that your dog has eaten the entire dose. This will minimize the potential for exposure to children or other household members to LAVERDIA.
• Return any unused LAVERDIA tablets to your veterinarian.

What should I do in case of accidental contact when handling LAVERDIA?
• In case of contact with skin, wash the affected area immediately and thoroughly with soap and water.
• In the case of accidental eye exposure:
o Rinse the eyes with large amounts of tap water (use eyewash station if present) for 10 minutes while holding back the eyelid.
o Remove contact lenses.
o Seek medical advice immediately and show the package insert, label, or client information sheet to the physician.

• If LAVERDIA is accidentally ingested, seek medical advice immediately. If there is significant contact with feces, urine, vomit, or saliva from your dog during treatment, or within 3 days after the last treatment, without proper precautions, seek medical advice immediately. It is important to show the treating physician a copy of the package insert, label, or client information sheet.

How do I safely clean up after my dog during treatment with LAVERDIA?Because LAVERDIA is a cancer treatment drug, extra care must be taken when cleaning up after your dog during treatment and for 3 days after the last treatment with LAVERDIA.
• Avoid direct contact with feces, urine, vomit, or saliva during treatment and for 3 days after the dog has completed treatment with LAVERDIA.
• Any skin that comes in contact with feces, urine, vomit, or saliva should be washed immediately with soap and water.
• When cleaning up feces, urine, vomit, or saliva you should wear protective disposable chemotherapy resistant gloves and collect the contaminated material with disposable absorptive material (such as paper towels) and place them into a plastic bag. Carefully remove the gloves and place them in the bag and tie or fasten it securely. Wash your hands thoroughly afterwards.
• You should not wash any items soiled with feces, urine, vomit, or saliva from your dog with other laundry during treatment and for 3 days after the dog has completed treatment.
• Do not let your dog urinate or defecate in areas where people may come in direct contact with the urine or feces.
• Children should not come in contact with the feces, urine, vomit, or saliva of treated dogs.
• If there is significant contact with feces, urine, vomit, or saliva from your dog during treatment, or within 3 days after the last treatment, without proper precautions, seek medical advice immediately. It is important to show the treating physician a copy of the package insert, label, or client information sheet.

Because LAVERDIA may be present in your dog's saliva during treatment and for 3 days after the last treatment, wear protective disposable chemotherapy resistant gloves when handling the dog’s toys, food bowl, and water bowl. Wash food and water bowls separately from other items.

LAVERDIA® is a trademark of Dechra Pharmaceuticals Limited. Dechra is a registered trademark of Dechra Pharmaceuticals Limited.

Manufactured for:
Dechra Veterinary Products, LLC
7015 College Boulevard, Suite 525 Overland Park, KS 66211
(866) 933-2472

Approved by FDA under NADA # 141-614

Issued 01/2026

PPT-7002-04

PACKAGE LABEL

PRINCIPAL DISPLAY PANEL - 2.5 mg Carton

2.5 mg

NDC 17033-021-01

LAVERDIA®
(verdinexor tablets)

2.5 mg per tablet

Antineoplastic
For Oral Use in Dogs Only

Indicated for the treatment of lymphoma in dogs

CAUTION: Federal law restricts this drug to use by or on the order of a licensed veterinarian.

Approved by FDA under NADA # 141-614

NET CONTENTS

16 tablets

Dechra

PRINCIPAL DISPLAY PANEL - 10 mg Carton

10 mg

NDC 17033-022-01

LAVERDIA®
(verdinexor tablets)

10 mg per tablet

Antineoplastic
For Oral Use in Dogs Only

Indicated for the treatment of lymphoma in dogs

CAUTION: Federal law restricts this drug to use by or on the order of a licensed veterinarian.

Approved by FDA under NADA # 141-614

NET CONTENTS

16 tablets

Dechra

PRINCIPAL DISPLAY PANEL - 50 mg Carton

50 mg

NDC 17033-024-01

LAVERDIA®
(verdinexor tablets)

50 mg per tablet

Antineoplastic
For Oral Use in Dogs Only

Indicated for the treatment of lymphoma in dogs

CAUTION: Federal law restricts this drug to use by or on the order of a licensed veterinarian.

Approved by FDA under NADA # 141-614

NET CONTENTS

16 tablets

Dechra